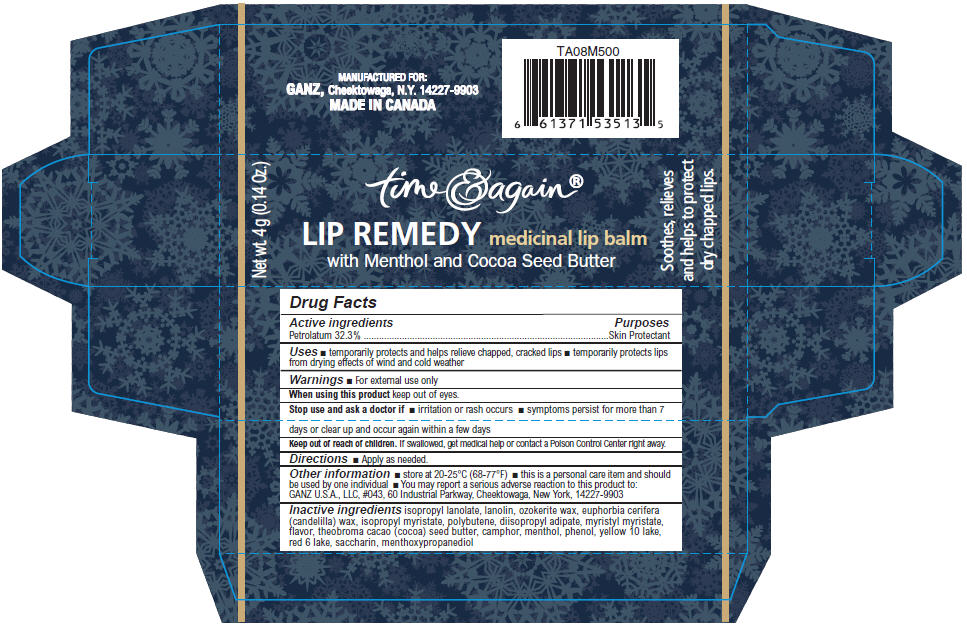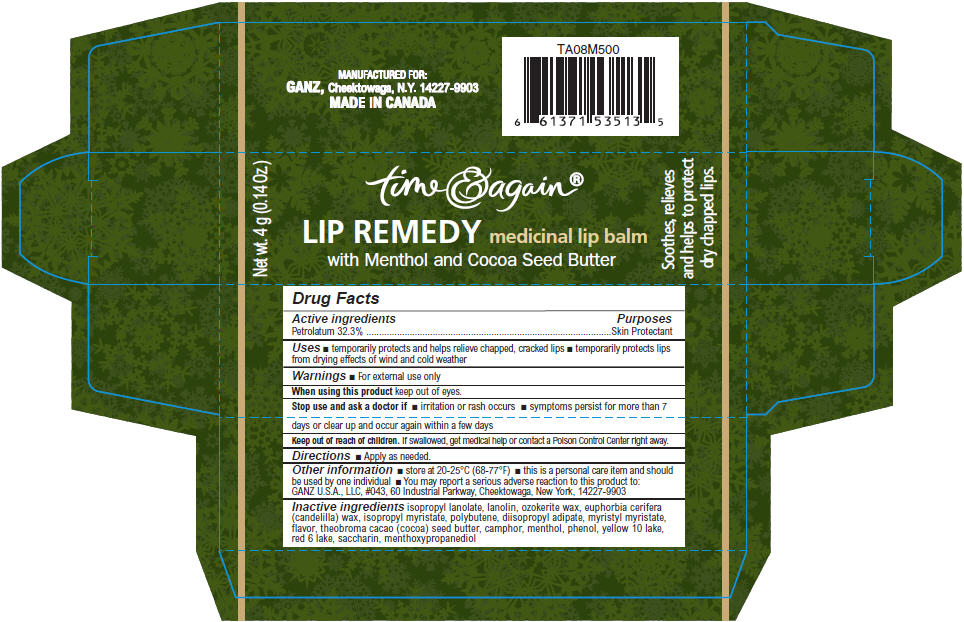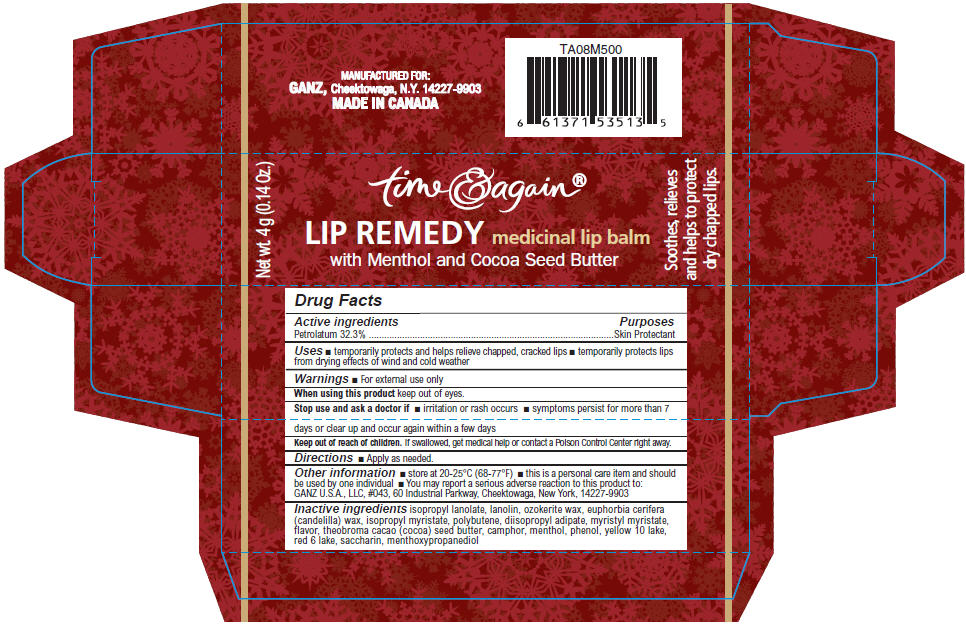 DRUG LABEL: Lip Remedy Medicinal Lip Balm 
NDC: 55143-012 | Form: STICK
Manufacturer: Norwood Packaging Ltd.
Category: otc | Type: HUMAN OTC DRUG LABEL
Date: 20110322

ACTIVE INGREDIENTS: PETROLATUM 32.3 g/100 g
INACTIVE INGREDIENTS: LANOLIN; CERESIN; CANDELILLA WAX; ISOPROPYL MYRISTATE; DIISOPROPYL ADIPATE; MYRISTYL MYRISTATE; COCOA BUTTER; CAMPHOR (SYNTHETIC); MENTHOL; PHENOL; D&C YELLOW NO. 10; D&C RED NO. 6; ALUMINUM OXIDE; SACCHARIN

time & again®
LIP REMEDY medicinal lip balm
with Menthol and Cocoa Seed Butter

Drug Facts

Active ingredients

Petrolatum 32.3%

Purposes

Skin Protectant

Uses

- temporarily protects and helps relieve chapped, cracked lips
- temporarily protects lips from drying effects of wind and cold weather

Warnings

- For external use only

When using this product keep out of eyes.

Stop use and ask a doctor if

- irritation or rash occurs
- symptoms persist for more than 7 days or clear up and occur again within a few days

Keep out of reach of children. If swallowed, get medical help or contact a Poison Control Center right away.

Directions

- Apply as needed.

Other information

STORAGE AND HANDLING

- store at 20-25°C (68-77°F)

- this is a personal care item and should be used by one individual
- You may report a serious adverse reaction to this product to: GANZ U.S.A., LLC, #043, 60 Industrial Parkway, Cheektowaga, New York, 14227-9903

Inactive ingredients

isopropyl lanolate, lanolin, ozokerite wax, euphorbia cerifera (candelilla) wax, isopropyl myristate, polybutene, diisopropyl adipate, myristyl myristate, flavor, theobroma cacao (cocoa) seed butter, camphor, menthol, phenol, yellow 10 lake, red 6 lake, saccharin, menthoxypropanediol

PRINCIPAL DISPLAY PANEL - 4 g Blue Carton

Net wt. 4 g (0.14 Oz.)

time & again®
LIP REMEDY medicinal lip balm
with Menthol and Cocoa Seed Butter

Soothes, relieves
and helps to protect
dry chapped lips.

PRINCIPAL DISPLAY PANEL - 4 g Green Carton

Net wt. 4 g (0.14 Oz.)

time & again®
LIP REMEDY medicinal lip balm
with Menthol and Cocoa Seed Butter

Soothes, relieves
and helps to protect
dry chapped lips.

PRINCIPAL DISPLAY PANEL - 4 g Red Carton

Net wt. 4 g (0.14 Oz.)

time & again®
LIP REMEDY medicinal lip balm
with Menthol and Cocoa Seed Butter

Soothes, relieves
and helps to protect
dry chapped lips.